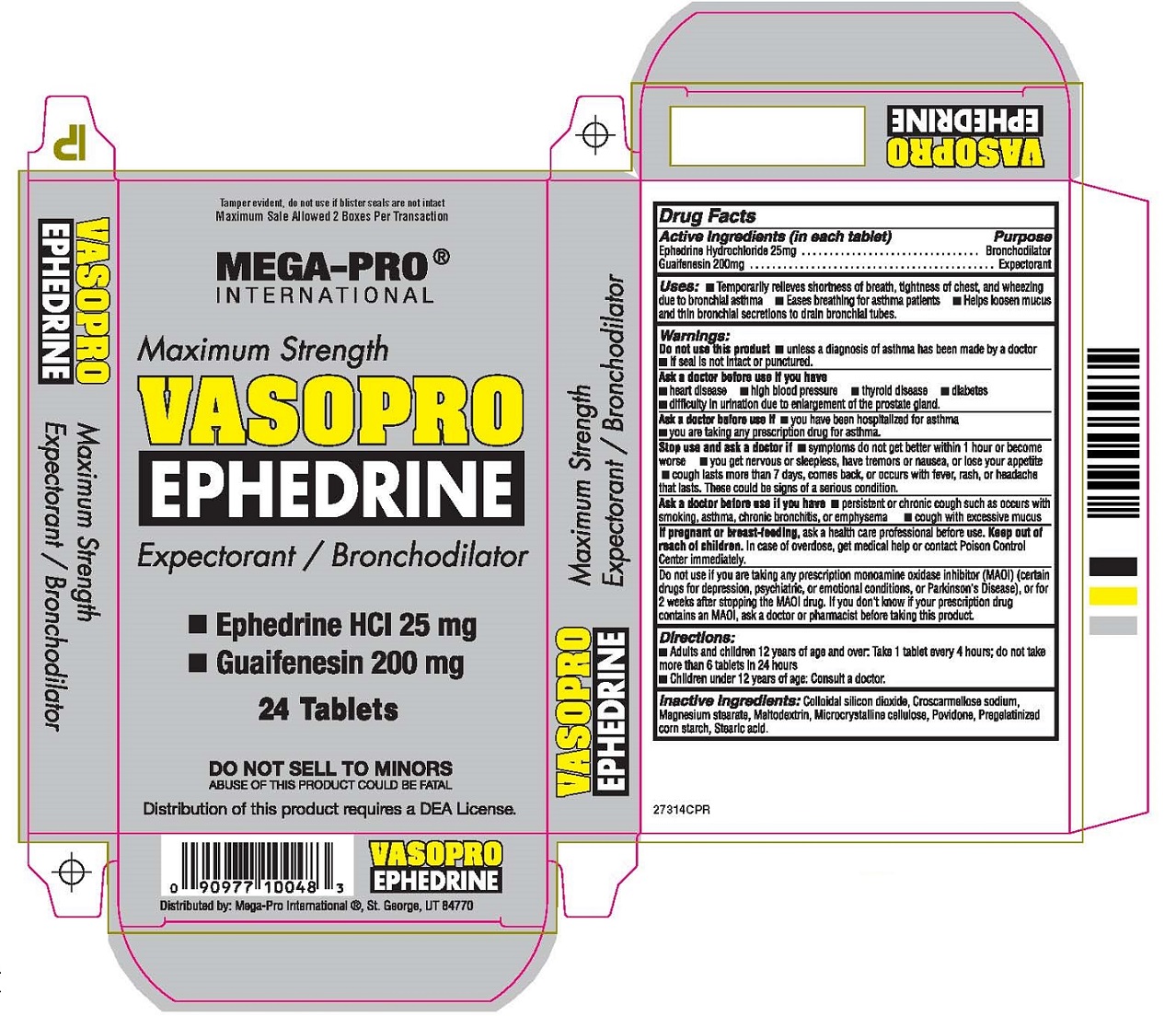 DRUG LABEL: VASOPRO EPHEDRINE
NDC: 70258-320 | Form: TABLET
Manufacturer: Optimal Research Inc
Category: otc | Type: HUMAN OTC DRUG LABEL
Date: 20151123

ACTIVE INGREDIENTS: EPHEDRINE HYDROCHLORIDE 25 mg/1 1; GUAIFENESIN 200 mg/1 1
INACTIVE INGREDIENTS: COLLOIDAL SILICON DIOXIDE; CROSCARMELLOSE SODIUM; MAGNESIUM STEARATE; MALTODEXTRIN; CELLULOSE, MICROCRYSTALLINE; POVIDONE; STARCH, CORN; STEARIC ACID

VASOPRO EPHEDRINE expectorant / Bronchodilator

Active Ingredients (in each tablet)

Ephedrine Hydrochloride 25mg

Guaifenesin 200mg

Purpose

Bronchodilator

Expectorant

Keep out of reach of children. In case of overdose, get medical help or contact Poison Control Center immediately.

INDICATIONS AND USAGE

Uses: • Temporarily relieves shortness of breath, tightness of chest, and wheezing due to bronchial asthma

• Eases breathing for asthma patients • Helps loosen mucus and thin bronchial secretions to drain bronchial tubes.

Warnings:

Do not use this product • unless a diagnosis of asthma has been made by a doctor
• If seal is not intact or punctured.

Ask a doctor before use if you have
• heart disease • high blood pressure • thyroid disease • diabetes
• difficulty in urination due to enlargement of the prostate gland.

Ask a doctor before use if • you have been hospitalized for asthma

• you are taking any prescription drug for asthma.

Stop use and ask a doctor if • symptoms do not get better within 1 hour or become worse

• you get nervous or sleepless, have tremors or nausea, or lose your appetite

• cough lasts more than 7 days, comes back, or occurs with fever, rash, or headache that lasts.

These could be signs of a serious condition.

Ask a doctor before use if you have • persistent or chronic cough such as occurs with smoking, asthma,

chronic bronchitis, or emphysema • cough with excessive mucus

If pregnant or breast-feeding, ask a health care professional before use.

Do not use if you are taking any prescription monoamine oxidase inhibitor (MAOI) (certain drugs for depression,

psychiatric, or emotional conditions, or Parkinson’s Disease), or for 2 weeks after stopping the MAOI drug.

If you don’t know if your prescription drug contains an MAOI, ask a doctor or pharmacist before taking this product.

Directions:

• Adults and children 12 years of age and over. Take 1 tablet every 4 hours: do not take more than 6 tablets in 24 hours

• Children under 12 years of age: Consult a doctor.

INACTIVE INGREDIENT

Inactive Ingredients: Colloidal silicon dioxide, Croscarmellose sodium, Magnesium stearate, Maltodextrin, Microcrystalline cellulose

Povidone, Pregelatinized corn starch, Stearic acid.

Tamper evident, do not use if blister seals are not intact
Maximum Sale Allowed 2 Boxes Per Transaction

MEGA-PRO®
INTERNATIONAL

Maximum Strength
VASOPRO
EPHEDRINE
Expectorant / Bronchodilator
24 Tablets

DO NOT SELL TO MINORS
ABUSE OF THIS PRODUCT COULD BE FATAL

Distribution of this product requires a DEA License.

Distributed by: Mega-Pro International®, St. George, UT 84770